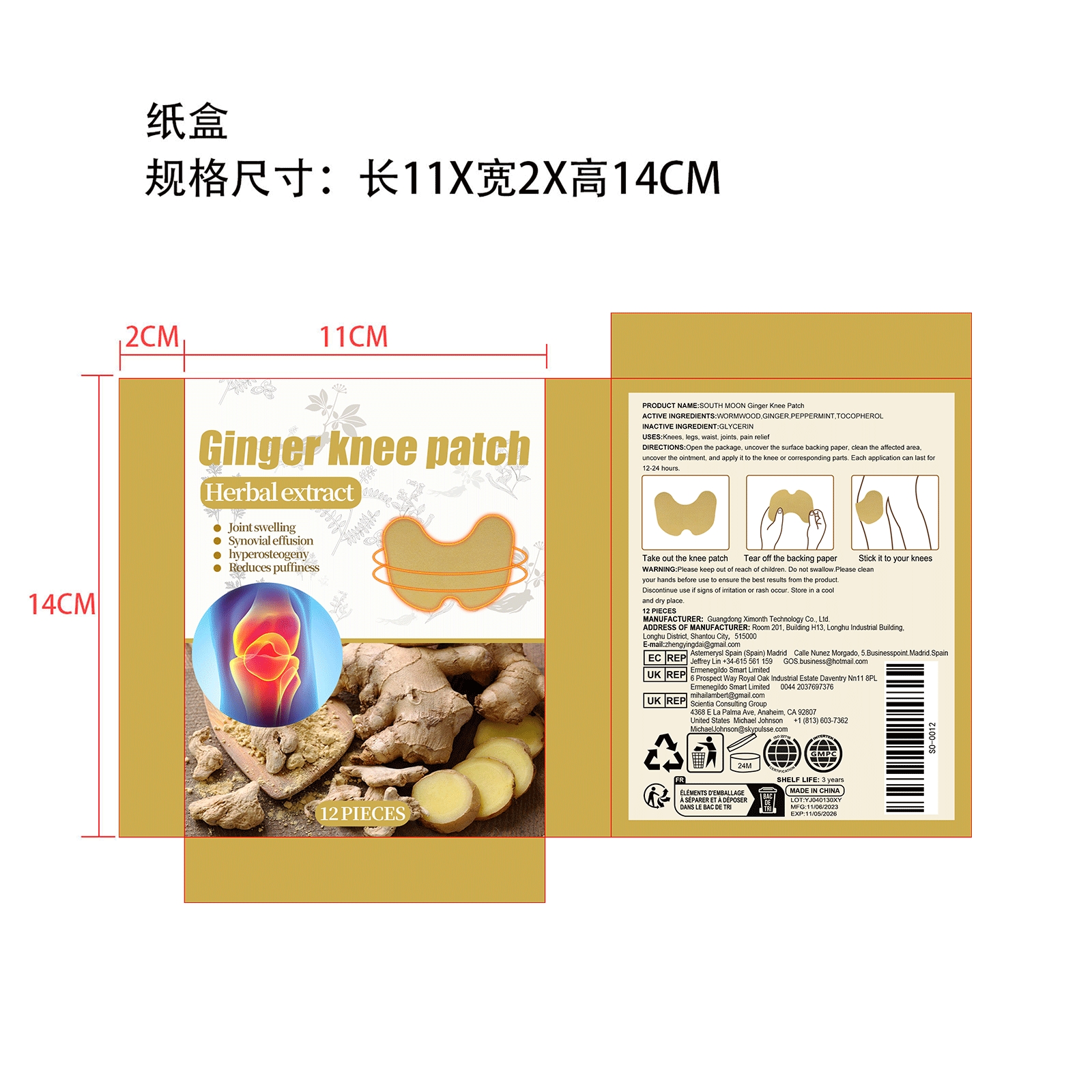 DRUG LABEL: SOUTH MOON Ginger Knee Patch
NDC: 84660-053 | Form: PATCH
Manufacturer: Guangdong Ximonth Technology Co., Ltd.
Category: otc | Type: HUMAN OTC DRUG LABEL
Date: 20241030

ACTIVE INGREDIENTS: TOCOPHEROL 5.55 g/37 g; PEPPERMINT 5.55 g/37 g; WORMWOOD 11.1 g/37 g; GINGER 3.7 g/37 g
INACTIVE INGREDIENTS: GLYCERIN 11.1 g/37 g

ACTIVE INGREDIENTS

WORMWOOD,GINGER,PEPPERMINT,TOCOPHEROL

PURPOSE

Knees, legs, waist, joints, pain relief

USES

Open the package, uncover the surface backingpaper, clean the affected area, uncover the ointment, and apply it to the knee orcorresponding parts. Each application can last for 12-24 hours.

WARNING

Please keep out of reach of children. Do not swallow.Please cleanyour hands before use to ensure the best results from the product.Discontinue use if signs of irritation or rash occur. Store in a cool and dry place.

STOP USE

Discontinue use if signs of irritation or rash occur.

DO NOT USE

Discontinue use if signs of irritation or rash occur.

KEEP OUT OF REACH OF CHILDREN

Please keep out of reach of children. Do not swallow.

STORAGE AND HANDLING

Store in a cool and dry place.

INACTIVE INGREDIENT

GLYCERIN